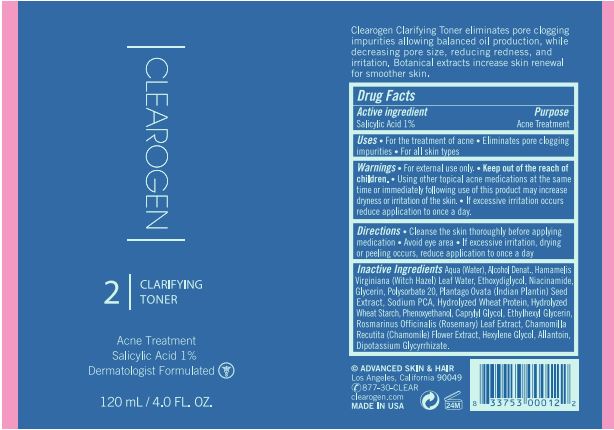 DRUG LABEL: Clarifying Toner
NDC: 62742-4240 | Form: LIQUID
Manufacturer: Allure Labs
Category: otc | Type: HUMAN OTC DRUG LABEL
Date: 20231208

ACTIVE INGREDIENTS: SALICYLIC ACID 1 g/100 g
INACTIVE INGREDIENTS: ROSEMARY; MATRICARIA RECUTITA FLOWERING TOP; ALLANTOIN; CAPRYLYL GLYCOL; ETHYLHEXYLGLYCERIN; PLANTAGO OVATA SEED; DIETHYLENE GLYCOL MONOETHYL ETHER; STARCH, WHEAT; HEXYLENE GLYCOL; HAMAMELIS VIRGINIANA LEAF WATER; ALCOHOL; PHENOXYETHANOL; SODIUM PYRROLIDONE CARBOXYLATE; WATER; HYDROLYZED WHEAT PROTEIN (ENZYMATIC, 3000 MW); GLYCYRRHIZINATE DIPOTASSIUM; NIACINAMIDE; GLYCERIN; POLYSORBATE 20

Drug Facts

Active Ingredient:

Salicylic Acid 1%

Purpose: Acne Treatment

INDICATIONS AND USAGE

Uses: For the treatment of acne

Gently cleanses and maintains optimal moisture balance.

For all skin types

WARNINGS

Warning: For external use only

DO NOT USE

If excessive dryness or peeling occurs.

WHEN USING

Avoid eye area.

STOP USE

If excessive dryness or peeling occurs.

Keep out of reach of children.

DOSAGE AND ADMINISTRATION

Direction:

Cleanse the skin thoroughly before applying medication. Avoid eye area. If excessive dryness or peeling occurs, reduce application to once a day.

OTHER SAFETY INFORMATION

Using other topical acne medication at the same time or immediately following use of this product may increase dryness or irritation of the skin.If this occurs, only one medication should be used unless directed by a doctor.

Inactive Ingredient:

Water (Aqua), Alcohol Denat, Hamamelis Virginiana (Witch Hazel) Leaf Water, Ethoxydiglycol, Niacinamide, Glycerin, Polysorbate 20, Plantago Ovata (Indian Plantin) Seed Extract, Sodium PCA, Hydrolyzed Wheat Protein, Hydrolyzed Wheat Starch, Phenoxyethanol, Caprylyl Glycol, Ethylhexyl Glycerin, Rosmarinus Officinalis (Rosemary) Leaf Extract, Chamomilla Recutita (Chamomile) Flower Extract, Hexylene Glycol, Allantoin, Dipotassium Glycyrrhizate.